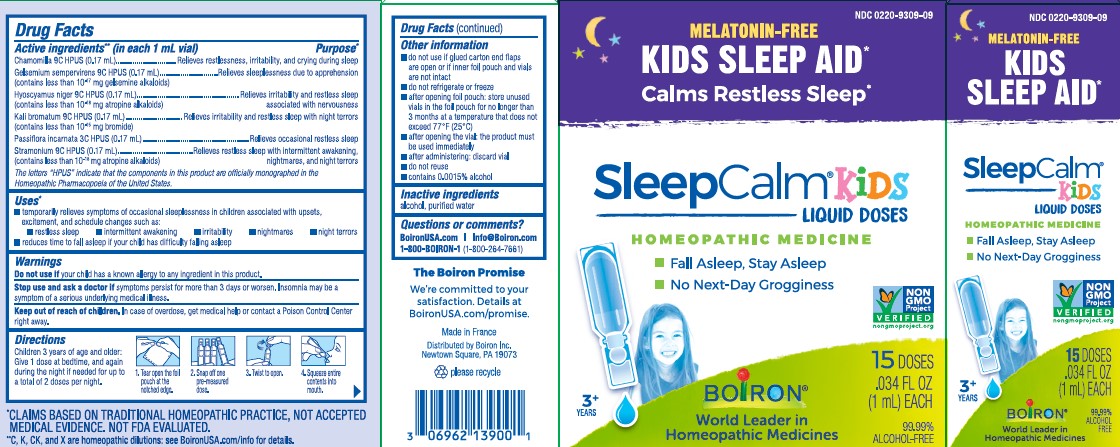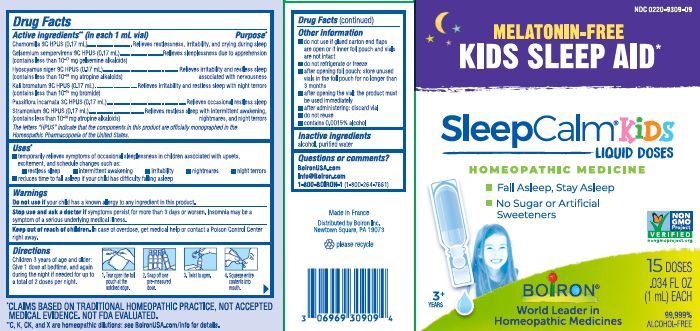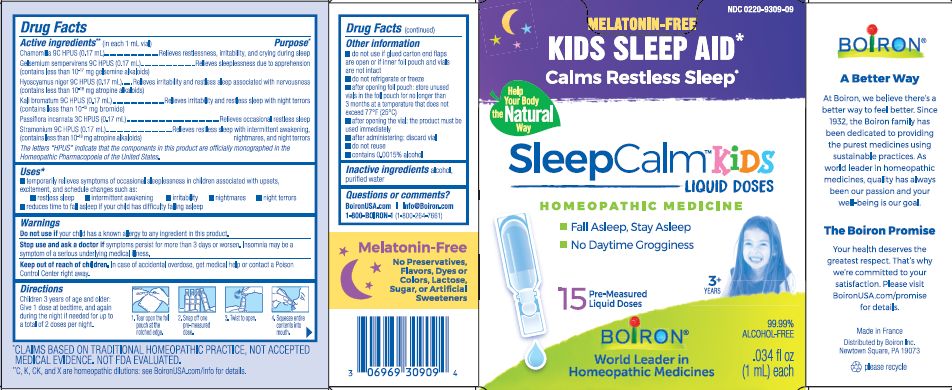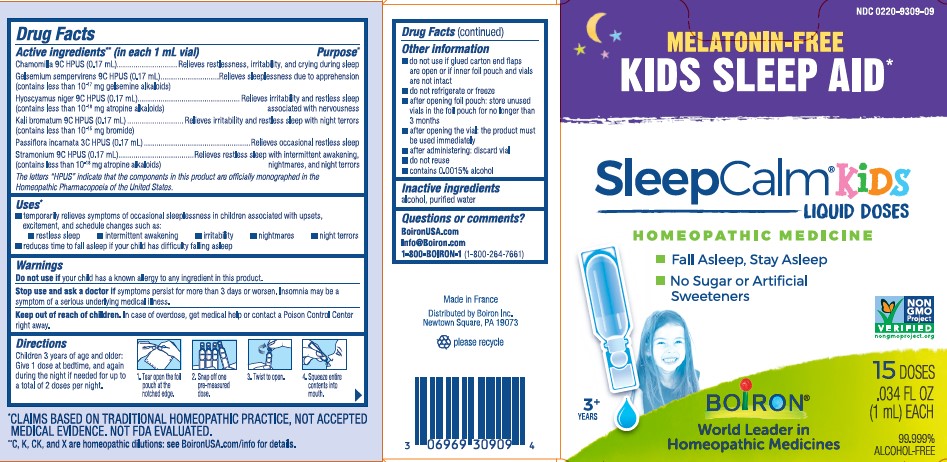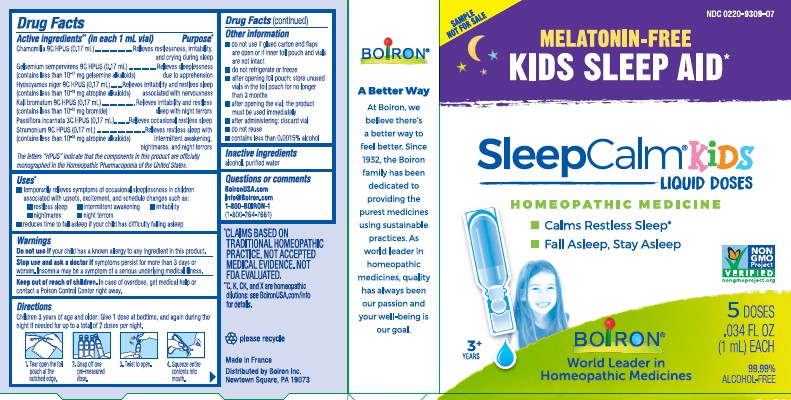 DRUG LABEL: SleepCalm Kids
NDC: 0220-9309 | Form: LIQUID
Manufacturer: Boiron
Category: homeopathic | Type: HUMAN OTC DRUG LABEL
Date: 20240809

ACTIVE INGREDIENTS: DATURA STRAMONIUM 9 [hp_C]/1 1; POTASSIUM BROMIDE 9 [hp_C]/1 1; PASSIFLORA INCARNATA FLOWERING TOP 3 [hp_C]/1 1; MATRICARIA CHAMOMILLA WHOLE 9 [hp_C]/1 1; GELSEMIUM SEMPERVIRENS ROOT 9 [hp_C]/1 1; HYOSCYAMUS NIGER 9 [hp_C]/1 1
INACTIVE INGREDIENTS: WATER; ALCOHOL

SleepCalm Kids

Active ingredients** (in each 1 mL vial)

Chamomilla 9C HPUS (0.17 mL)

Gelsemium sempervirens 9C HPUS (0.17 mL) (contains less than 10^-17 mg gelsemine alkaloids)

Hyoscyamus niger 9C HPUS (0.17mL) (contains less than 10^-18 mg atropine alkaloids)

Kali bromatum 9C HPUS (0.17mL) (contains less than 10^-15 mg bromide)

Passiflora incarnata 3C HPUS (0.17 mL)

Starmonium 9C HPUS (0.17 mL) (contains less than 10^-18 mg atropine alkaloids)

The letters "HPUS" indicate that the components in this product are officially monographed in the Homeopathic Pharmacopoeia of the United States.

Purpose*

Chamomilla 9C HPUS ... Relieves restlessness, irritability, and crying during sleep

Gelsemium sempervirens 9C HPUS ... Relieves sleeplessness due to apprehension

Hyoscyamus niger 9C HPUS ... Relieves irritability and restless sleep associated with nervousness

Kali bromatum 9C HPUS ... Relieves irritability and restless sleep with night terrors

Passiflora incarnata 3C HPUS ... Relieves occasional restless sleep

Starmonium 9C HPUS ... Relieves restless sleep with intermittent awakening, nightmares and night terrors

Uses*

- temporarily relieves symptoms of occasional sleeplessness in children associated with upsets, excitement, and schedule changes such as:
- restless sleep
- intermittent awakening
- irritability
- nightmares
- night terrors
- reduces the time to fall asleep if your child has difficulty falling asleep

Do not use if your child has a known allergy to any ingredient in this product.

STOP USE

Stop and use and ask a doctor if symptoms persist for more than 3 days or worsen. Insomnia may be a symptom of a serious underlying medical illness.

Keep out of reach of children. In case of accidental overdose, get medical help or contact a Poison Control Center right away.

DOSAGE AND ADMINISTRATION

Children 3 years of age and older: Give 1 dose at bedtime, and again during the night if needed for up to a total of 2 doses per night.

Tear open the foil pouch at the notched edge. Snap off one pre-measured dose. Twist to open. Squeeze entire contents into mouth.

do not use if glued carton end flaps are open or if inner foil pouch and vials are not intact

do not refrigerate or freeze

after opening the foil pouch: store unused vials in the foil pouch for no longer than 3 months

after opening the vial: the product must be used immediately

after administering: discard vial

do not reuse

contains 0.0015% alcohol

Calms Restless Sleep*

Kids Sleep Aid*

Melatonin Free

15 pre-measured liquid doses

5 pre-measured liquid doses

0.34 fl oz (1 mL) each

99.99% alcohol-free

Fall Asleep, Stay Asleep

*CLAIMS BASED ON TRADITIONAL HOMEOPATHIC PRACTICE, NOT ACCEPTED MEDICAL EVIDENCE. NOT FDA EVALUATED.

*C,K,CK, and X are homeopathic dilutions: see BoironUSA.com/info for details.

INACTIVE INGREDIENT

alcohol, purified water,

QUESTIONS

BoironUSA.com Info@boiron.com

1-800-BOIRON-1 (1-800-264-7661)

Distributed by Boiron, Inc. Newtown Square, PA 19073

Made in France